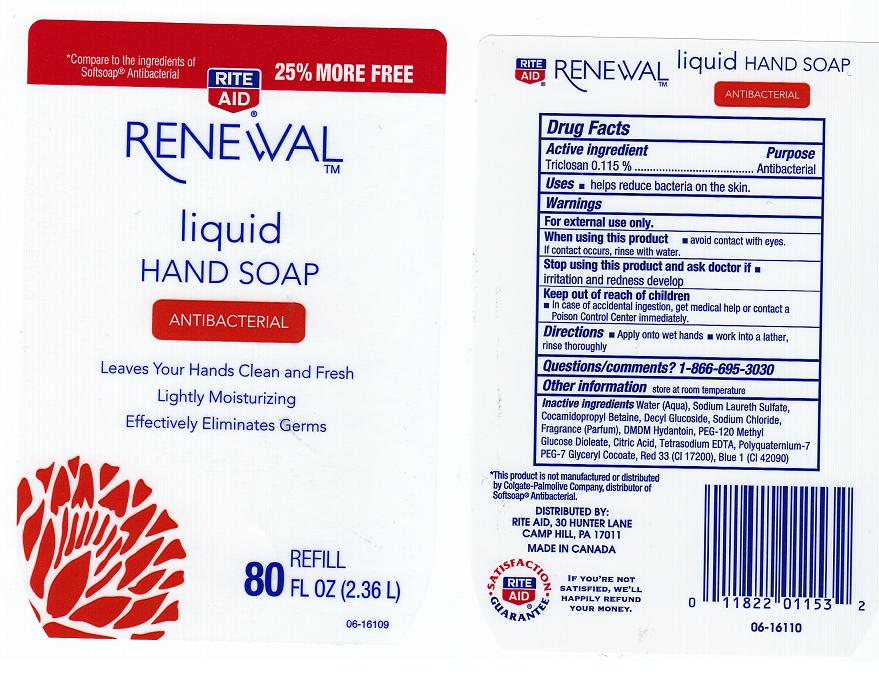 DRUG LABEL: RITE AID
NDC: 11822-7208 | Form: LIQUID
Manufacturer: RITE AID CORPORATION
Category: otc | Type: HUMAN OTC DRUG LABEL
Date: 20120224

ACTIVE INGREDIENTS: TRICLOSAN 0.115 mL/100 mL
INACTIVE INGREDIENTS: WATER; SODIUM LAURETH SULFATE; COCAMIDOPROPYL BETAINE; DECYL GLUCOSIDE; SODIUM CHLORIDE; DMDM HYDANTOIN; PEG-120 METHYL GLUCOSE DIOLEATE; CITRIC ACID MONOHYDRATE; EDETATE SODIUM; POLYQUATERNIUM-7 (70/30 ACRYLAMIDE/DADMAC; 1600 KD); PEG-7 GLYCERYL COCOATE; D&C RED NO. 33; FD&C BLUE NO. 1

DRUG FACTS

ACTIVE INGREDIENT

TRICLOSAN 0.115%

PURPOSE

ANTIBACTERIAL

USES

HELPS REDUCE BACTERIA ON THE SKIN.

WARNINGS

FOR EXTERNAL USE ONLY.

WHEN USING THIS PRODUCT

AVOID CONTACT WITH EYES. IF CONTACT OCCURS, RINSE WITH WATER.

STOP USING THIS PRODUCT AND ASK DOCTOR IF

IRRITATION AND REDNESS DEVELOP.

KEEP OUT OF REACH OF CHILDREN

IN CASE OF ACCIDENTAL INGESTION, GET MEDICAL HELP OR CONTACT A POISON CONTROL CENTER IMMEDIATELY.

DIRECTIONS

APPLY ONTO WET HANDS. WORK INTO A LATHER, RINSE THOROUGHLY.

QUESTIONS/COMMENTS?

1-866-695-3030

OTHER INFORMATION

STORE AT ROOM TEMPERATURE.

INACTIVE INGREDIENTS

WATER (AQUA), SODIUM LAURETH SULFATE, COCAMIDOPROPYL BETAINE, DECYL GLUCOSIDE, SODIUM CHLORIDE, FRAGRANCE (PARFUM), DMDM HYDANTOIN, PEG-120 METHYL GLUCOSE DIOLEATE, CITRIC ACID, TETRASODIUM EDTA, POLYQUATERNIUM-7, PEG-7 GLYCERYL COCOATE, RED 33 (CI 17200), BLUE 1 (CI 42090).